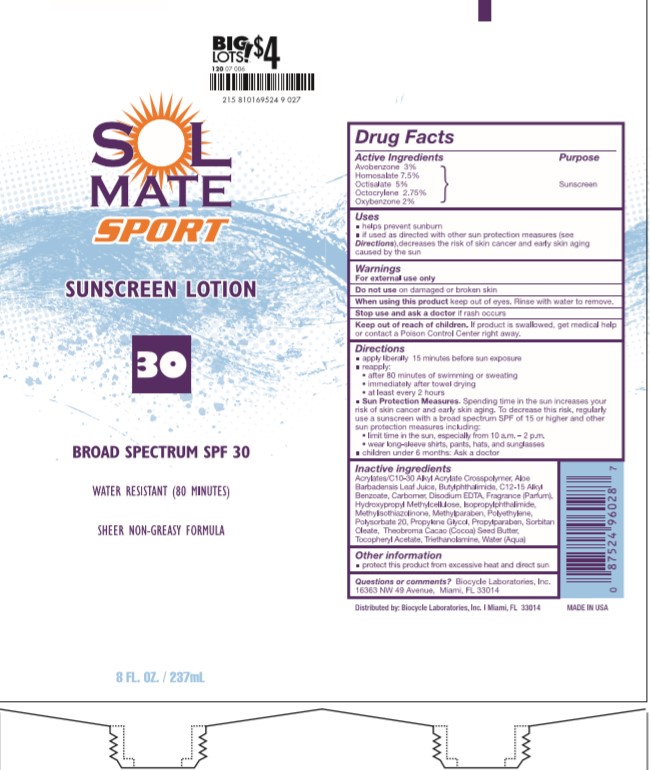 DRUG LABEL: Solmate
NDC: 58443-0171 | Form: LOTION
Manufacturer: Prime Enterprises Inc.
Category: otc | Type: HUMAN OTC DRUG LABEL
Date: 20201021

ACTIVE INGREDIENTS: OCTOCRYLENE 26.95 mg/1 mL; HOMOSALATE 73.5 mg/1 mL; OCTISALATE 49 mg/1 mL; AVOBENZONE 29.4 mg/1 mL; OXYBENZONE 19.6 mg/1 mL
INACTIVE INGREDIENTS: FRAGRANCE LAVENDER & CHIA F-153480; ALOE VERA LEAF; METHYLISOTHIAZOLINONE; N-BUTYLPHTHALIMIDE; ISOPROPYLPHTHALIMIDE; CARBOMER HOMOPOLYMER, UNSPECIFIED TYPE; EDETATE DISODIUM ANHYDROUS; TROLAMINE; WATER; METHYLPARABEN; PROPYLENE GLYCOL; PROPYLPARABEN; SORBITAN MONOOLEATE; POLYSORBATE 20; ALKYL (C12-15) BENZOATE; CARBOMER INTERPOLYMER TYPE A (ALLYL SUCROSE CROSSLINKED); HYPROMELLOSES; HIGH DENSITY POLYETHYLENE; COCOA BUTTER; ALPHA-TOCOPHEROL ACETATE

Solmate Sport Sunscreen Lotion Broad Spectrum SPF 30

Active Ingredients

Avobenzone 3%, Homosalate 7.5%, Octisalate 5%, Octocrylene 2.75%, Oxybenzone 2%

Uses

helps prevent sunburn

if used as directed with other sun protection measures (see Directions), decreases the risk of skin cancer and early skin aging caused by the sun

Warnings

For external use only

Do not use

on damaged or broken skin

when using this product

keep out of eyes. Rinse with water to remove.

Stop use and ask a doctor

if rash occurs

Keep out of reach of children.

If product is swallowed, get medical help or contact a Poison Control Center right away.

Directions

apply liberally 15 minutes before sun exposure

reapply:

- after 80 minutes of swimming or sweating
- immediately after towel drying
- at least every 2 hours

Sun Protection Measures. Spending time in the sun increases your risk of skin cancer and early skin aging. To decrease this risk, regularly use a sunscreen with a broad spectrum SPF of 15 or higher and other sun protection measures including:

- limit time in the sun, especially form 10 a.m. - 2 p.m.
- wear long-sleeve shirts, pants, hats, and sunglasses

children under 6 months: Ask a doctor

Inactive ingredients

Acrylates/C10-30 Alkyl Acrylate Crosspolymer, Aloe Barbadensis Leaf Juice, Butylphthalimide, C12-15 Alkyl Benzoate, Carbomer, Disodium EDTA, Fragrance (Parfum), Hydroxypropyl Methylcellulose, Isopropylphthalimide, Methylisothiazolinone, Methylparaben, Polyethylene, Polysorbate 20, Propylene Glycol, Propylparaben, Sorbitan Oleate, Theobroma Cacao (Cocoa) Seed Butter, Tocopheryl Acetate, Triethanolamine, Water (Aqua)

Other information

protect ths product from excessive heat and direct sun

Questions or comments?:

Biocycle Laboratories, Inc. 16363 NW 49 Avenue, Miami, FL 33014